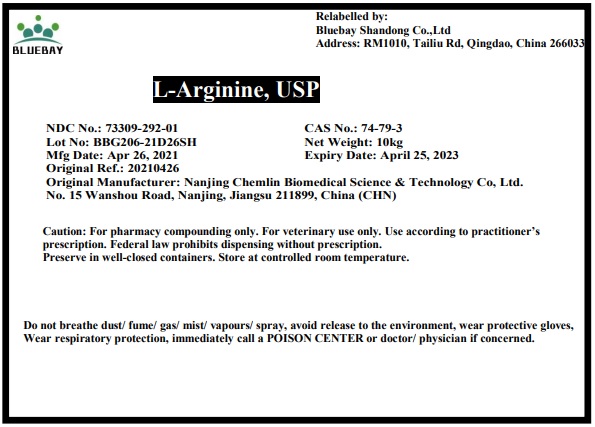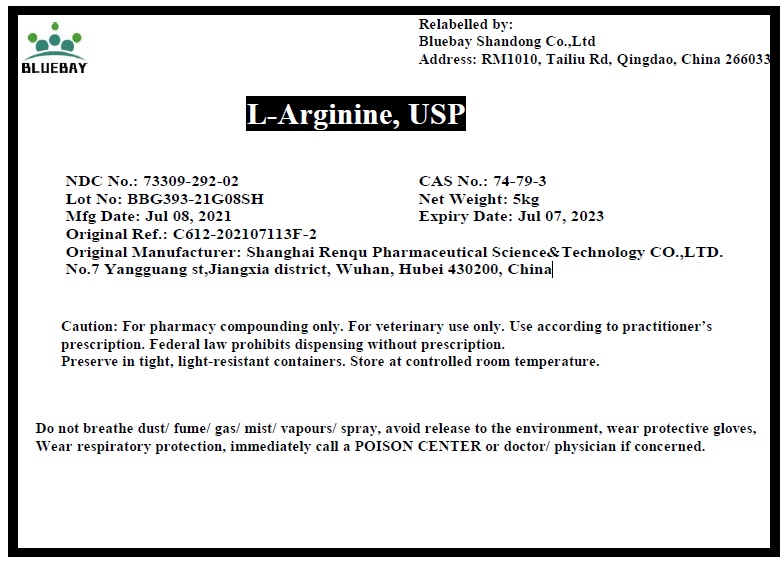 DRUG LABEL: L-Arginine
NDC: 73309-292 | Form: POWDER
Manufacturer: BLUEBAY SHANDONG CO.,LTD
Category: other | Type: BULK INGREDIENT
Date: 20210804

ACTIVE INGREDIENTS: ARGININE 1 kg/1 kg

L-Arginine